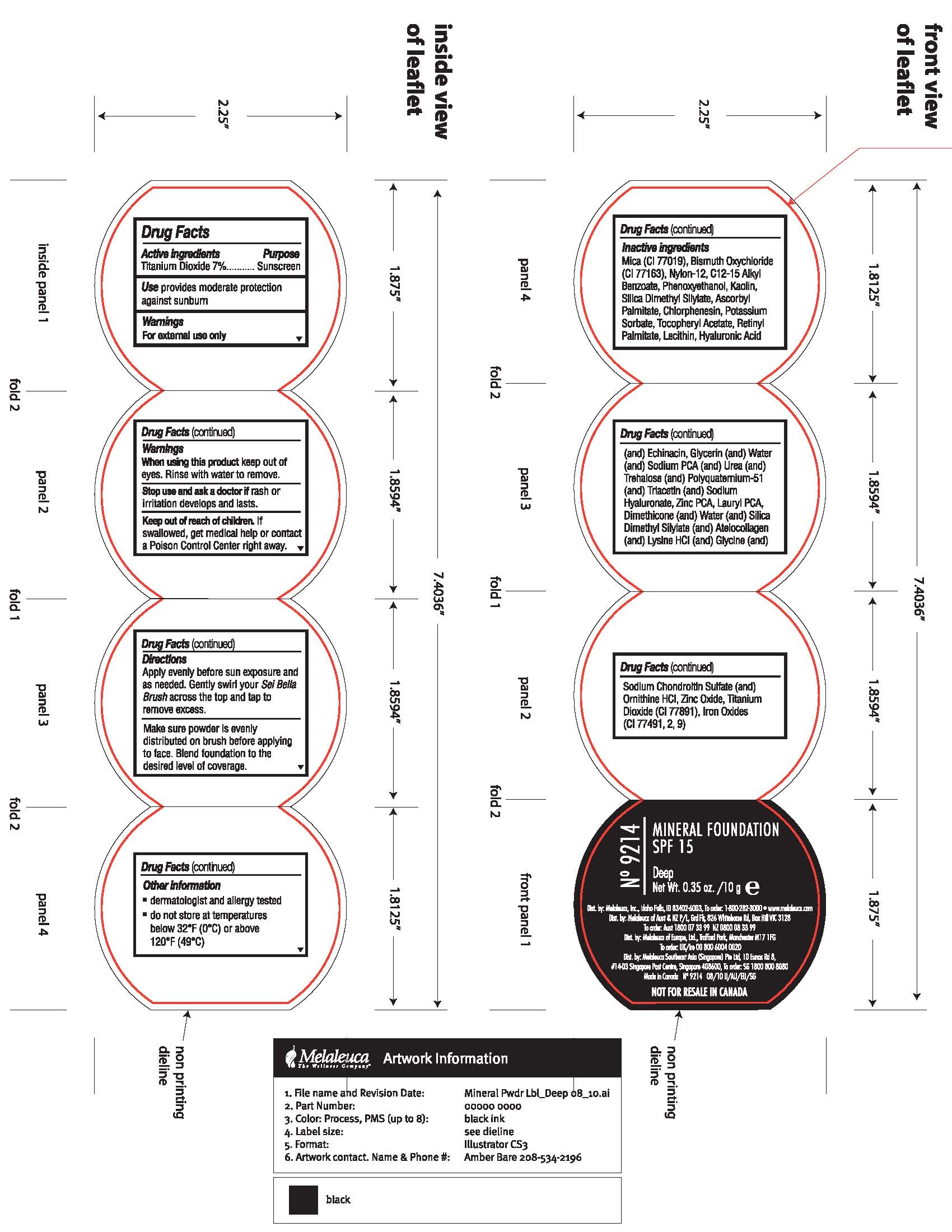 DRUG LABEL: SPF 15
NDC: 54473-179 | Form: POWDER
Manufacturer: Melaleuca, Inc.
Category: otc | Type: HUMAN OTC DRUG LABEL
Date: 20101214

ACTIVE INGREDIENTS: TITANIUM DIOXIDE 0.7 g/10 g
INACTIVE INGREDIENTS: MICA; BISMUTH OXYCHLORIDE; PHENOXYETHANOL; KAOLIN; ASCORBYL PALMITATE; CHLORPHENESIN; POTASSIUM SORBATE; VITAMIN A PALMITATE; LECITHIN, SOYBEAN; HYALURONIC ACID; GLYCERIN; WATER; UREA; TREHALOSE; TRIACETIN; DIMETHICONE; LYSINE HYDROCHLORIDE; GLYCINE; CHONDROITIN SULFATE (PORCINE); ZINC OXIDE; TITANIUM DIOXIDE; ALPHA-TOCOPHEROL ACETATE; C12-15 ALKYL BENZOATE; SODIUM PYRROLIDONE CARBOXYLATE; HYALURONATE SODIUM; ORNITHINE HYDROCHLORIDE; FERRIC OXIDE YELLOW; FERRIC OXIDE RED; FERROSOFERRIC OXIDE; ZINC PIDOLATE; SILICON DIOXIDE

Label of Mineral Foundation Deep

Directions

Apply evenly before sun exposure as needed. Gently swirl your Sei Bella Brush across the top and tap to remove excess.

Make sure powder is evenly distributed on brush before applying to face. Blend foundation to the desired level of coverage.

Other Information

- dermatologist and allergy tested

Other Information

- do not store at temperatures below 32°F (0° or above 120°F (49°C)

INACTIVE INGREDIENT

Ingredients

Mica (CI 77019), Bismuth Oxichloride (CI 77163), Nylon-12, C12-15 Alkyl Benzoate, Phenoxyethanol, Kaolin, Silica Dimethyl Silylate, Ascorbyl Palmitate, Chlorphensin, Potassium Sorbate, Retinyl Palmitate, Lecithin, Hyaluronic Acid (and) Echinacin, Glycerin (and) Water (and) Urea (and) Trehalose (and) Polyquaternium-51 (and) Triacetin (and) Sodium Hyaluronate, Zinc PCA, Lauryl PCA, Dimethicone (and) Water (and) Silica Dimethyl Silylate (and) Ateloollagen (and) Lysine HCI (and) Glycine (and) Sodium Chondrotin Sulfate (and) Ornithine HCI, Zinc Oxide, Titanium Dioxide (CI 77891), Iron Oxides (CI 77491, 2, 9)

Active Ingredients Purpose

Titanium Dioxide 7%...........Sunscreen